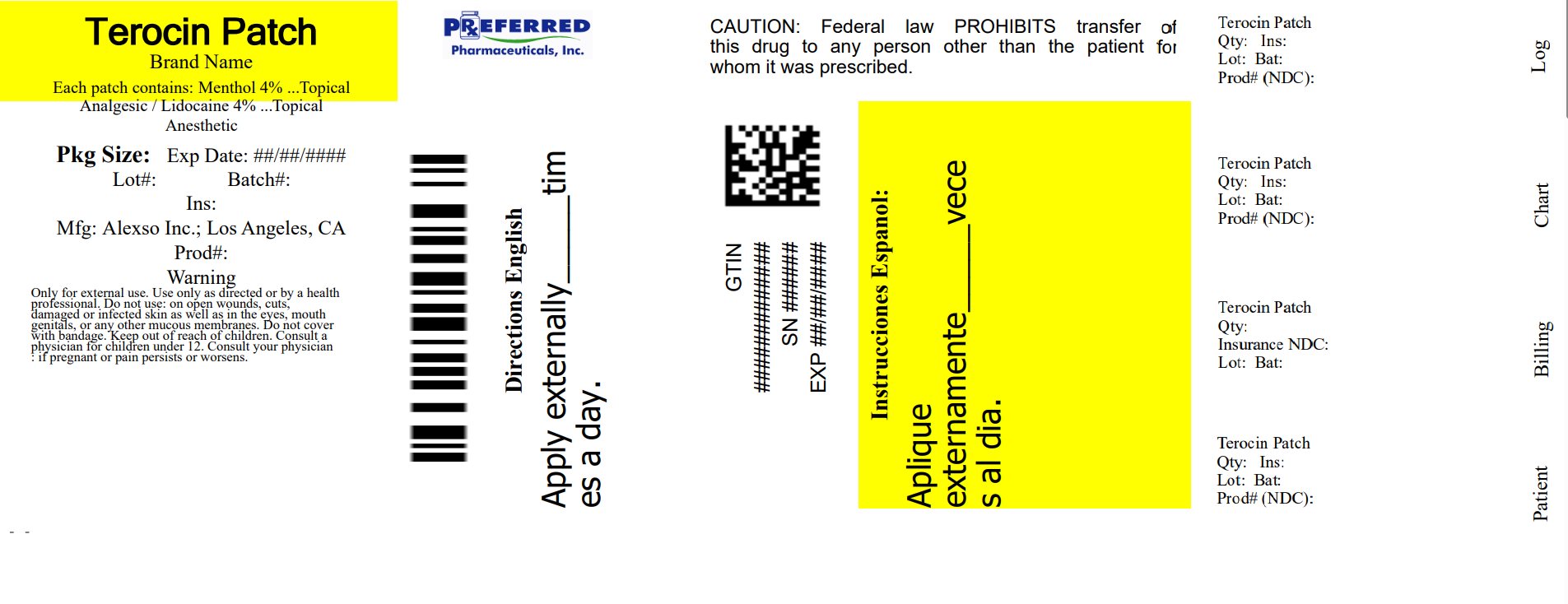 DRUG LABEL: Terocin
NDC: 68788-9555 | Form: PATCH
Manufacturer: Preferred Pharmaceuticals, Inc.
Category: otc | Type: HUMAN OTC DRUG LABEL
Date: 20250930

ACTIVE INGREDIENTS: LIDOCAINE 600 mg/1 1; MENTHOL, UNSPECIFIED FORM 600 mg/1 1
INACTIVE INGREDIENTS: WATER; GLYCERIN; SODIUM POLYACRYLATE (2500000 MW); POLYSORBATE 80; LEMON OIL, COLD PRESSED; ALOE VERA LEAF; EDETATE DISODIUM; DIAZOLIDINYL UREA; METHYLPARABEN; IODOPROPYNYL BUTYLCARBAMATE; PROPYLPARABEN

Terocin Patch

Terocin Patch

Active ingredients:

Menthol 4%

Purpose

Topical Analgesic

Active ingredients:

Lidocaine 4%

Purpose

Topical Anesthetic

Uses:

For the temporarily relief of minor aches and muscle pains associated with arthritis, simple backache, strains, muscle soreness and stiffness.

Warnings:

- Only for external use. Use only as directed or by a health professional.
- Do not use: on open wounds, cuts, damaged or infected skin as well as in the eyes, mouth, genitals, or any other mucous membranes.
- Do not cover with bandage.
- Consult your physician: if pregnant or pain persists or worsens.

Keep out of reach of children.

Consult physician for children under 12.

Directions:

Adults and childred 12 years and over: Apply patch to affected area 1 to 2 times daily or as directed.

Instructions for use:

- Clean and dry the affected area
- Open pouch and remove one patch
- Remove any protective film and apply directly to affected area of pain
- Wash hands with soap and water after applying patch
- Reseal pouch containing unused patches after each use

Other Ingredients:

Water, Glycerine, Sodium Polyacrylate, Polysorbate 80, Lemon Oil, Diazolidinyl Urea, Aloe Vera Leaf, Propylparaben, Methylparaben, Iodopropynyl Butylcarbamate, Edetate Disodium

- Manufactured for: Alexso Inc.
  2317 Cotner Avenue
  Los Angeles, CA 90064

Store in a dry, cool place
For Comments or Questions, call 888-495-6078

Patent Pending

Package Insert

This topical pain relief patch was recently reformulated by pharmacists who specialize in pain management. Natural ingredients have been added to these patches for a better, more refreshing smell. Scientific studies have shown that both ingredients used in this product significantly reduce pain and inflammation.i A combination of ingredients with analgesics and anesthetic properties are used in a unique way to maximize its pain relieving effects and to aid in addition to other therapies. This offers long lasting relief for a variety of pain conditions. Terocin Patch is manufactured in accordance with FDA regulations by an FDA approved manufacturer.

Active Ingredients:

Menthol 4%
Lidocaine 4%

Uses:

This formulation can be used to assist patients in the treatment of mild to moderate acute or chronic aches or pain. Muscle or joint pain can be due to musculoligamentous strains, simple backache, tendonitis, osteoarthritis, rheumatoid arthritis, peripheral neuropathies such as diabetic neuropathy or post herpetic neuralgia, and other complex regional pains. It can also be used to help with certain types of headaches but use with caution when applying in order to avoid eye contact.ii If consulted by your physician, it may be used for other conditions as well.

Directions:

- Adults and children 12 years and over: Apply patch to affected area 1 to 2 times daily or as directed.
- Instructions for Use:
  - Clean and dry the affected area
  - Open pouch and remove one patch
  - Remove any protective film and apply directly to affected area of pain
  - Wash hands with soap and water after applying patch
  - Reseal pouch containing unused patches after each use
  - Pain relief varies from patient to patient; may need to use a few times to see benefit.

Mechanism of Action:

Menthol has some local anesthetic and counterirritant qualities and also acts as a weak kappa opioid receptor agonist making it an analgesic as well. Its ability to chemically trigger the cold-sensitive TRPM8 receptors in the skin is responsible for its cooling sensation when applied to the skin. Lastly, it enhances the efficacy of other topical applications by increasing penetration via vasodilation.

Lidocaine is a common local anesthetic that relieves itching, burning, and pain. Topically, it blocks both initiation and conduction of nerve impulses by decreasing ionic flux through the neuronal membrane. Since it penetrates the skin, it creates an anesthetic effect by not just preventing pain signals from propagating to the brain but by stopping them before they begin.

Benefits: The use of this topical medication, Terocin Patch, over other oral options for pain relief can benefit patients in many different ways. Conventional therapies using opioids (hydrocodone, hydromorphone, morphine, oxycodone) can cause systemic adverse effects such as constipation, drowsiness, dizziness, lightheadedness, nausea, vomiting, sedation, and/or confusion. NSAIDs (ibuprofen, naproxen) can increase cardiovascular risk, decrease platelet aggregation, and cause gastrointestinal bleeding or ulcers. Other classes of medications such as antidepressants (nortriptyline, duloxetine) or anticonvulsants (gabapentin) also come with its costs and side effects. Terocin Patch acts only locally since it penetrates the skin and not into the bloodstream. In addition, patients can have one or multiple disease states including renal or hepatic dysfunction which can prevent them from taking ibuprofen (Advil) or acetaminophen (Tylenol) respectively. More importantly, this patch gives physicians an option to provide effective pain relief treatment while avoiding the addictive properties of conventional oral medications. It can also be supplemented with other topical pain lotions. In addition, it avoids messy application and reduces risk of getting ingredients in eyes or other mucous membranes.

Product Information and Data: Pharmacists that have been in the field of pain management for many years used research from all parts of the world to carefully formulate this patch in order to maximize its pain relieving properties.iii Skin penetrating mixtures have also been added to enhance rapid absorption of the active ingredients through the skin to allow deeper penetration into the muscles, joints, and nerves. Lidocaine patches for therapy of neuropathic and non-neuropathic pain was concluded “to be an effective and safe option for add-on therapy” (Nervenarzt, 2010) in a clinical case series using 87 patients.iv Another study in 2010 concluded that a single 8 hour application of a combination patch of menthol provided significant pain relief associated with mild to moderate strains when compared to a placebo patch.v The use of these pharmaceutical and natural components provides more pain relief and makes the patch a new way to address pain. These ingredients comply with The Chronic Pain Medical Treatment Guidelines and the ACOEM guidelines for pain management.vi Page 111 of the Chronic Pain Medical Treatment Guidelines concludes that topical analgesics are “primarily recommended for neuropathic pain when trials of antidepressants and anticonvulsants have failed (Namaka, 2004).” In addition to this, “these agents are applied locally to painful areas with advantages that include lack of systemic side effects, absence of drug interactions, and no need to titrate (Colombo, 2006).” This product is “recognized as safe and effective” because it meets all conditions of the CFR.vii Terocin Patch complies with The Chronic Pain Medical Treatment Guidelines and the ACOEM guidelines for a variety of pains mentioned above.viii

Adverse Reactions: Even though adverse reactions are rare, a very small percentage of patients experience an unpleasant burning sensation, redness, warmth, or stinging. Please be aware of any unpleasant side effects as described. If any of these effects persists or worsens, contact your physician or pharmacist immediately. This medication is not absorbed systemically but if any serious side effects (i.e. rash, itching/swelling, severe dizziness) are experienced, discontinue use immediately and contact your pharmacist or physician. This is not a complete list of all side effects that may occur. You may report side effects to the FDA at 800-FDA-1088 or at http://www.fda.gov/medwatch.

Warnings:

- Only for external use only. Use only as directed or by a health professional.
- Do not use: on open wounds, cuts, damaged or infected skin as well as in the eyes, mouth, genitals, or any other mucus membranes.
- Do not cover with bandage.
- Keep away from children. Consult physician for children under 12 years.
- Consult your physician: if pregnant or if pain persists or worsens
- Consult your physician: if pain persist or worsens or if using any other topical pain products.
- Store in a dry, cool place

In Case of Ingestion or Overdose, get medical help or contact a Poison Control Center (800-222-1222) right away.

Inactive Ingredients:

Water, Glycerine, Sodium Polyacrylate, Polysorbate 80, Citrus Medica Limonum (Lemon) Peel Oil, Aloe Barbadesis Leaf (Aloe Vera Gel) Juice, EDTA Disodium salt, Diazolidinyl Urea, Methylparaben, Iodoproynyl Butylcabamate, Propylparaben.

i Dunteman E. Targeted peripheral analgesics in Chronic Pain Syndromes. Practical Pain Management 2005; July/August: 14-25.

ii Jones M. Chronic neuropathic pain: Pharmacologic interventions in the new millennium. A theory of efficacy. International J Pharmaceutical Compounding. 2004(1):6-15.

iii Baron R, Mahn F. Types of topical treatment for peripheral neuropathic pain: Mechanism of action and indications. Schmerz 2010;24(4):317-25.

iv Kern KU, Kohl M, Kiefer RT. Lidocaine patch for therapy of neuropathic and non-neuropathic pain. A clinical case series of 87 patients. Nervenarzt 2010 Dec;81(12): 1490-7.

v Higashi Y, Kiuchi T, Furuta K. Efficacy and safety profile of a topical methyl salicylate and menthol patch in adult patients with mild to moderate muscle strain: a randomized, double-blind, parallel-group, placebo-controlled, multicenter study. Clinical Therapeutics. 2010 Jan;32(1): 34-43.

vi ACOEM. Occupational Medicine Practice Guidelines, 2nd Edition. American College of Occupational and Environmental Medicine, 25 Northwest Point Blvd., Suite 700, Elk Grove Village, Illinois, 60007-1030 (www.acoem.org.). 2004:116.

vii CFR – Code of Federal Regulations. Food and Drug Administration. Chapter 1: Part 346. Revised April 1, 2010.

viii Chronic Pain Medical Treatment Guidelines, Medical Treatment Utilization Schedule (MTUS). Effective July 18, 2009.

Topical Pain

Relief Patch

Alexso inc.

Relabeled By: Preferred Pharmaceuticals Inc.

Package/Label Principal Display Panel

Terocin Patch

Topical Pain Patch
for long lasting relief

NDC 68788-9555-1

Qty: 10 Articulated Patches
(5 per Resealable Pouch) x 2

Box Label